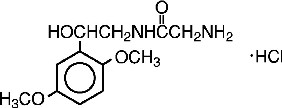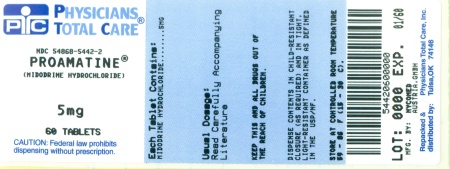 DRUG LABEL: ProAmatine
NDC: 54868-5442 | Form: TABLET
Manufacturer: Physicians Total Care, Inc.
Category: prescription | Type: HUMAN PRESCRIPTION DRUG LABEL
Date: 20100526

ACTIVE INGREDIENTS: MIDODRINE HYDROCHLORIDE 5 mg/1 1
INACTIVE INGREDIENTS: SILICON DIOXIDE; STARCH, CORN; FD&C YELLOW NO. 6; MAGNESIUM STEARATE; CELLULOSE, MICROCRYSTALLINE; TALC

BOXED WARNING

Warning: Because ProAmatine® can cause marked elevation of supine blood pressure, it should be used in patients whose lives are considerably impaired despite standard clinical care. The indication for use of ProAmatine® in the treatment of symptomatic orthostatic hypotension is based primarily on a change in a surrogate marker of effectiveness, an increase in systolic blood pressure measured one minute after standing, a surrogate marker considered likely to correspond to a clinical benefit. At present, however, clinical benefits of ProAmatine®, principally improved ability to carry out activities of daily living, have not been verified.

DESCRIPTION

Name: ProAmatine®(midodrine hydrochloride) Tablets

Dosage Form: 2.5-mg, 5-mg and 10-mg tablets for oral administration

Active Ingredient: Midodrine hydrochloride, 2.5 mg, 5 mg and 10 mg

Inactive Ingredients: Colloidal Silicone Dioxide NF, Corn Starch NF, FD&C Blue No. 2 Lake (10-mg tablets), FD&C Yellow No. 6 Lake (5-mg tablet), Magnesium Stearate NF, Microcrystalline Cellulose NF, Talc USP

Pharmacological Classification: Vasopressor/Antihypotensive

Chemical Names (USAN: Midodrine Hydrochloride): (1) Acetamide, 2-amino-N-[2-(2,5-dimethoxyphenyl)-2-hydroxyethyl]-monohydrochloride, (±)-;

(2) (±)-2-amino-N-(β-hydroxy-2,5-dimethoxyphenethyl)acetamide monohydrochloride

BAN, INN, JAN: Midodrine

Structural formula:

Molecular formula: C12H18N2O4HCl; Molecular Weight: 290.7

Organoleptic Properties: Odorless, white, crystalline powder

Solubility: Water: Soluble

Methanol: Sparingly soluble

pKa: 7.8 (0.3% aqueous solution) pH: 3.5 to 5.5 (5% aqueous solution)

Melting Range: 200 to 203°C

CLINICAL PHARMACOLOGY

Mechanism of Action: ProAmatine® forms an active metabolite, desglymidodrine, that is an alpha1-agonist, and exerts its actions via activation of the alpha-adrenergic receptors of the arteriolar and venous vasculature, producing an increase in vascular tone and elevation of blood pressure. Desglymidodrine does not stimulate cardiac beta-adrenergic receptors. Desglymidodrine diffuses poorly across the blood-brain barrier, and is therefore not associated with effects on the central nervous system.

Administration of ProAmatine® results in a rise in standing, sitting, and supine systolic and diastolic blood pressure in patients with orthostatic hypotension of various etiologies. Standing systolic blood pressure is elevated by approximately 15 to 30 mmHg at 1 hour after a 10-mg dose of midodrine, with some effect persisting for 2 to 3 hours. ProAmatine® has no clinically significant effect on standing or supine pulse rates in patients with autonomic failure.

Pharmacokinetics: ProAmatine® is a prodrug, i.e., the therapeutic effect of orally administered midodrine is due to the major metabolite desglymidodrine, formed by deglycination of midodrine. After oral administration, ProAmatine® is rapidly absorbed. The plasma levels of the prodrug peak after about half an hour, and decline with a half-life of approximately 25 minutes, while the metabolite reaches peak blood concentrations about 1 to 2 hours after a dose of midodrine and has a half-life of about 3 to 4 hours. The absolute bioavailability of midodrine (measured as desglymidodrine) is 93%. The bioavailability of desglymidodrine is not affected by food. Approximately the same amount of desglymidodrine is formed after intravenous and oral administration of midodrine. Neither midodrine nor desglymidodrine is bound to plasma proteins to any significant extent.

Metabolism and Excretion: Thorough metabolic studies have not been conducted, but it appears that deglycination of midodrine to desglymidodrine takes place in many tissues, and both compounds are metabolized in part by the liver. Neither midodrine nor desglymidodrine is a substrate for monoamine oxidase.

Renal elimination of midodrine is insignificant. The renal clearance of desglymidodrine is of the order of 385 mL/minute, most, about 80%, by active renal secretion. The actual mechanism of active secretion has not been studied, but it is possible that it occurs by the base-secreting pathway responsible for the secretion of several other drugs that are bases (see also Potential for Drug Interactions).

Clinical Studies

Midodrine has been studied in 3 principal controlled trials, one of 3-weeks duration and 2 of 1 to 2 days duration. All studies were randomized, double-blind and parallel-design trials in patients with orthostatic hypotension of any etiology and supine-to-standing fall of systolic blood pressure of at least 15 mmHg accompanied by at least moderate dizziness/lightheadedness. Patients with pre-existing sustained supine hypertension above 180/110 mmHg were routinely excluded. In a 3-week study in 170 patients, most previously untreated with midodrine, the midodrine-treated patients (10 mg t.i.d., with the last dose not later than 6 P.M.) had significantly higher (by about 20 mmHg) 1-minute standing systolic pressure 1 hour after dosing (blood pressures were not measured at other times) for all 3 weeks. After week 1, midodrine-treated patients had small improvements in dizziness/lightheadedness/unsteadiness scores and global evaluations, but these effects were made difficult to interpret by a high early drop-out rate (about 25% vs 5% on placebo). Supine and sitting blood pressure rose 16/8 and 20/10 mmHg, respectively, on average.

In a 2-day study, after open-label midodrine, known midodrine responders received midodrine 10 mg or placebo at 0, 3, and 6 hours. One-minute standing systolic blood pressures were increased 1 hour after each dose by about 15 mmHg and 3 hours after each dose by about 12mmHg; 3-minute standing pressures were increased also at 1, but not 3, hours after dosing. There were increases in standing time seen intermittently 1 hour after dosing, but not at 3 hours.

In a 1-day, dose-response trial, single doses of 0, 2.5, 10, and 20 mg of midodrine were given to 25 patients. The 10- and 20-mg doses produced increases in standing 1- minute systolic pressure of about 30 mmHg at 1 hour; the increase was sustained in part for 2 hours after 10 mg and 4 hours after 20 mg. Supine systolic pressure was =200 mmHg in 22% of patients on 10mg and 45% of patients on 20 mg; elevated pressures often lasted 6 hours or more.

Special Populations

A study with 16 patients undergoing hemodialysis demonstrated that ProAmatine® is removed by dialysis.

INDICATIONS AND USAGE

ProAmatine® is indicated for the treatment of symptomatic orthostatic hypotension (OH). Because ProAmatine® can cause marked elevation of supine blood pressure (BP>200 mmHg systolic), it should be used in patients whose lives are considerably impaired despite standard clinical care, including non-pharmacologic treatment (such as support stockings), fluid expansion, and lifestyle alterations. The indication is based on ProAmatine®'s effect on increases in 1-minute standing systolic blood pressure, a surrogate marker considered likely to correspond to a clinical benefit. At present, however, clinical benefits of ProAmatine®, principally improved ability to perform life activities, have not been established. Further clinical trials are underway to verify and describe the clinical benefits of ProAmatine®.

After initiation of treatment, ProAmatine® should be continued only for patients who report significant symptomatic improvement.

CONTRAINDICATIONS

ProAmatine® is contraindicated in patients with severe organic heart disease, acute renal disease, urinary retention, pheochromocytoma or thyrotoxicosis. ProAmatine® should not be used in patients with persistent and excessive supine hypertension.

WARNINGS

Supine Hypertension: The most potentially serious adverse reaction associated with ProAmatine® therapy is marked elevation of supine arterial blood pressure (supine hypertension). Systolic pressure of about 200 mmHg were seen overall in about 13.4% of patients given 10 mg of ProAmatine®. Systolic elevations of this degree were most likely to be observed in patients with relatively elevated pre-treatment systolic blood pressures (mean 170 mmHg). There is no experience in patients with initial supine systolic pressure above 180 mmHg, as those patients were excluded from the clinical trials. Use of ProAmatine® in such patients is not recommended. Sitting blood pressures were also elevated by ProAmatine® therapy. It is essential to monitor supine and sitting blood pressures in patients maintained on ProAmatine®.

PRECAUTIONS

General

The potential for supine and sitting hypertension should be evaluated at the beginning of ProAmatine® therapy. Supine hypertension can often be controlled by preventing the patient from becoming fully supine, i.e., sleeping with the head of the bed elevated. The patient should be cautioned to report symptoms of supine hypertension immediately. Symptoms may include cardiac awareness, pounding in the ears, headache, blurred vision, etc. The patient should be advised to discontinue the medication immediately if supine hypertension persists.

Blood pressure should be monitored carefully when ProAmatine® is used concomitantly with other agents that cause vasoconstriction, such as phenylephrine, ephedrine, dihydroergotamine, phenylpropanolamine, or pseudoephedrine.

A slight slowing of the heart rate may occur after administration of ProAmatine®, primarily due to vagal reflex. Caution should be exercised when ProAmatine® is used concomitantly with cardiac glycosides (such as digitalis), psychopharmacologic agents, beta blockers or other agents that directly or indirectly reduce heart rate. Patients who experience any signs or symptoms suggesting bradycardia (pulse slowing, increased dizziness, syncope, cardiac awareness) should be advised to discontinue ProAmatine® and should be re-evaluated.

ProAmatine® should be used cautiously in patients with urinary retention problems, as desglymidodrine acts on the alpha-adrenergic receptors of the bladder neck.

ProAmatine® should be used with caution in orthostatic hypotensive patients who are also diabetic, as well as those with a history of visual problems who are also taking fludrocortisone acetate, which is known to cause an increase in intraocular pressure and glaucoma.

ProAmatine® use has not been studied in patients with renal impairment. Because desglymidodrine is eliminated via the kidneys, and higher blood levels would be expected in such patients, ProAmatine® should be used with caution in patients with renal impairment, with a starting dose of 2.5 mg (see DOSAGE AND ADMINISTRATION). Renal function should be assessed prior to initial use of ProAmatine®.

ProAmatine® use has not been studied in patients with hepatic impairment. ProAmatine® should be used with caution in patients with hepatic impairment, as the liver has a role in the metabolism of midodrine.

Information for Patients

Patients should be told that certain agents in over-the-counter products, such as cold remedies and diet aids, can elevate blood pressure, and therefore, should be used cautiously with ProAmatine®, as they may enhance or potentiate the pressor effects of ProAmatine® (see Drug Interactions). Patients should also be made aware of the possibility of supine hypertension. They should be told to avoid taking their dose if they are to be supine for any length of time, i.e., they should take their last daily dose of ProAmatine® 3 to 4 hours before bedtime to minimize nighttime supine hypertension.

Laboratory Tests

Since desglymidodrine is eliminated by the kidneys and the liver has a role in its metabolism, evaluation of the patient should include assessment of renal and hepatic function prior to initiating therapy and subsequently, as appropriate.

Drug Interactions

When administered concomitantly with ProAmatine®, cardiac glycosides may enhance or precipitate bradycardia, A.V. block or arrhythmia.

The use of drugs that stimulate alpha-adrenergic receptors (e.g., phenylephrine, pseudoephedrine, ephedrine, phenylpropanolamine or dihydroergotamine) may enhance or potentiate the pressor effects of ProAmatine®. Therefore, caution should be used when ProAmatine® is administered concomitantly with agents that cause vasoconstriction.

ProAmatine® has been used in patients concomitantly treated with salt-retaining steroid therapy (i.e., fludrocortisone acetate), with or without salt supplementation. The potential for supine hypertension should be carefully monitored in these patients and may be minimized by either reducing the dose of fludrocortisone acetate or decreasing the salt intake prior to initiation of treatment with ProAmatine®. Alpha-adrenergic blocking agents, such as prazosin, terazosin, and doxazosin, can antagonize the effects of ProAmatine®.

Potential for Drug Interaction

It appears possible, although there is no supporting experimental evidence, that the high renal clearance of desyglymidodrine (a base) is due to active tubular secretion by the base-secreting system also responsible for the secretion of such drugs as metformin, cimetidine, ranitidine, procainamide, triamterene, flecainide, and quinidine. Thus there may be a potential for drug-drug interactions with these drugs.

Carcinogenesis, Mutagenesis, Impairment of Fertility

Long-term studies have been conducted in rats and mice at dosages 3 to 4 times the maximum recommended daily human dose on a mg/m^2 basis, with no indication of carcinogenic effects related to ProAmatine®. Studies investigating the mutagenic potential of ProAmatine® revealed no evidence of mutagenicity. Other than the dominant lethal assay in male mice, where no impairment of fertility was observed, there have been no studies on the effects of ProAmatine® on fertility.

Pregnancy

Pregnancy Category C. ProAmatine® increased the rate of embryo resorption, reduced fetal body weight in rats and rabbits, and decreased fetal survival in rabbits when given in doses 13 (rat) and 7 (rabbit) times the maximum human dose based on body surface area (mg/m^2). There are no adequate and well-controlled studies in pregnant women. ProAmatine® should be used during pregnancy only if the potential benefit justifies the potential risk to the fetus. No teratogenic effects have been observed in studies in rats and rabbits.

Nursing Mothers

It is not known whether this drug is excreted in human milk. Because many drugs are excreted in human milk, caution should be exercised when ProAmatine® is administered to a nursing woman.

Pediatric Use

Safety and effectiveness in pediatric patients have not been established.

ADVERSE REACTIONS

The most frequent adverse reactions seen in controlled trials were supine and sitting hypertension; paresthesia and pruritus, mainly of the scalp; goosebumps; chills; urinary urge; urinary retention and urinary frequency.

The frequency of these events in a 3-week placebo-controlled trial is shown in the following table:

Adverse Events
 | Placebo n=88 |  | Midodrine n=82
Event | # of reports | % of patients | # of reports | % of patients
Total # of reports | 22 |  | 77
Paresthesia^1 | 4 | 4.5 | 15 | 18.3
Piloerection | 0 | 0 | 11 | 13.4
Dysuria^2 | 0 | 0 | 11 | 13.4
Pruritis^3 | 2 | 2.3 | 10 | 12.2
Supine hypertension^4 | 0 | 0 | 6 | 7.3
Chills | 0 | 0 | 4 | 4.9
Pain^5 | 0 | 0 | 4 | 4.9
Rash | 1 | 1.1 | 2 | 2.4

^1 Includes hyperesthesia and scalp paresthesia

^2 Includes dysuria (1), increased urinary frequency (2), impaired urination (1), urinary retention (5), urinary urgency (2)

^3 Includes scalp pruritus

^4 Includes patients who experienced an increase in supine hypertension

^5 Includes abdominal pain and pain increase

Less frequent adverse reactions were headache; feeling of pressure/fullness in the head; vasodilation/flushing face; confusion/thinking abnormality; dry mouth; nervousness/anxiety and rash. Other adverse reactions that occurred rarely were visual field defect; dizziness; skin hyperesthesia; insomnia; somnolence; erythema multiforme; canker sore; dry skin; dysuria; impaired urination; asthenia; backache; pyrosis; nausea; gastrointestinal distress; flatulence and leg cramps.

The most potentially serious adverse reaction associated with ProAmatine® therapy is supine hypertension. The feelings of paresthesia, pruritus, piloerection and chills are pilomotor reactions associated with the action of midodrine on the alpha-adrenergic receptors of the hair follicles. Feelings of urinary urgency, retention and frequency are associated with the action of midodrine on the alpha-receptors of the bladder neck.

OVERDOSAGE

Symptoms of overdose could include hypertension, piloerection (goosebumps), a sensation of coldness and urinary retention. There are 2 reported cases of overdosage with ProAmatine®, both in young males. One patient ingested ProAmatine® drops, 250 mg, experienced systolic blood pressure greater than 200 mmHg, was treated with an IV injection of 20 mg of phentolamine, and was discharged the same night without any complaints. The other patient ingested 205 mg of ProAmatine® (41 5-mg tablets), and was found lethargic and unable to talk, unresponsive to voice but responsive to painful stimuli, hypertensive and bradycardic. Gastric lavage was performed, and the patient recovered fully by the next day without sequelae.

The single doses that would be associated with symptoms of overdosage or would be potentially life-threatening are unknown. The oral LD50 is approximately 30 to 50 mg/kg in rats, 675 mg/kg in mice, and 125 to 160 mg/kg in dogs.

Desglymidodrine is dialyzable.

Recommended general treatment, based on the pharmacology of the drug, includes induced emesis and administration of alpha-sympatholytic drugs (e.g., phentolamine).

DOSAGE AND ADMINISTRATION

The recommended dose of ProAmatine® is 10 mg, 3 times daily. Dosing should take place during the daytime hours when the patient needs to be upright, pursuing the activities of daily living. A suggested dosing schedule of approximately 4-hour intervals is as follows: shortly before, or upon arising in the morning, midday and late afternoon (not later than 6 P.M.). Doses may be given in 3-hour intervals, if required, to control symptoms, but not more frequently. Single doses as high as 20 mg have been given to patients, but severe and persistent systolic supine hypertension occurs at a high rate (about 45%) at this dose. In order to reduce the potential for supine hypertension during sleep, ProAmatine® should not be given after the evening meal or less than 4 hours before bedtime. Total daily doses greater than 30 mg have been tolerated by some patients, but their safety and usefulness have not been studied systematically or established. Because of the risk of supine hypertension, ProAmatine® should be continued only in patients who appear to attain symptomatic improvement during initial treatment.

The supine and standing blood pressure should be monitored regularly, and the administration of ProAmatine® should be stopped if supine blood pressure increases excessively.

Because desglymidodrine is excreted renally, dosing in patients with abnormal renal function should be cautious; although this has not been systematically studied, it is recommended that treatment of these patients be initiated using 2.5-mg doses.

Dosing in children has not been adequately studied.

Blood levels of midodrine and desglymidodrine were similar when comparing levels in patients 65 or older vs. younger than 65 and when comparing males vs. females, suggesting dose modifications for these groups are not necessary.

HOW SUPPLIED

ProAmatine® is supplied as 5-mg tablets for oral administration. The 5-mg tablet is orange, round, and biplanar, with a bevelled edge, and is scored on one side with "RPC" above and "5" below the score, and "004" on the other side.

5.0-milligram Tablets: NDC 54868-5442-0 Bottle of 10

NDC 54868-5442-2 Bottle of 60

NDC 54868-5442-1 Bottle of 90

Store at 25°C (77°F)

Excursions permitted to 15-30 °C (59-86 °F)

[see USP Controlled Room Temperature]

Manufactured for

Shire US Inc., One Riverfront Place, Newport, KY, 41071, USA

by NYCOMED Austria GmbH

© 2003 Shire US Inc.

Rev. 10/03

003 0107 006

Rx only

Repackaging and Relabeling by:
Physicians Total Care, Inc.
Tulsa, OK 74146

PRINCIPAL DISPLAY PANEL

ProAmatine®

5 mg